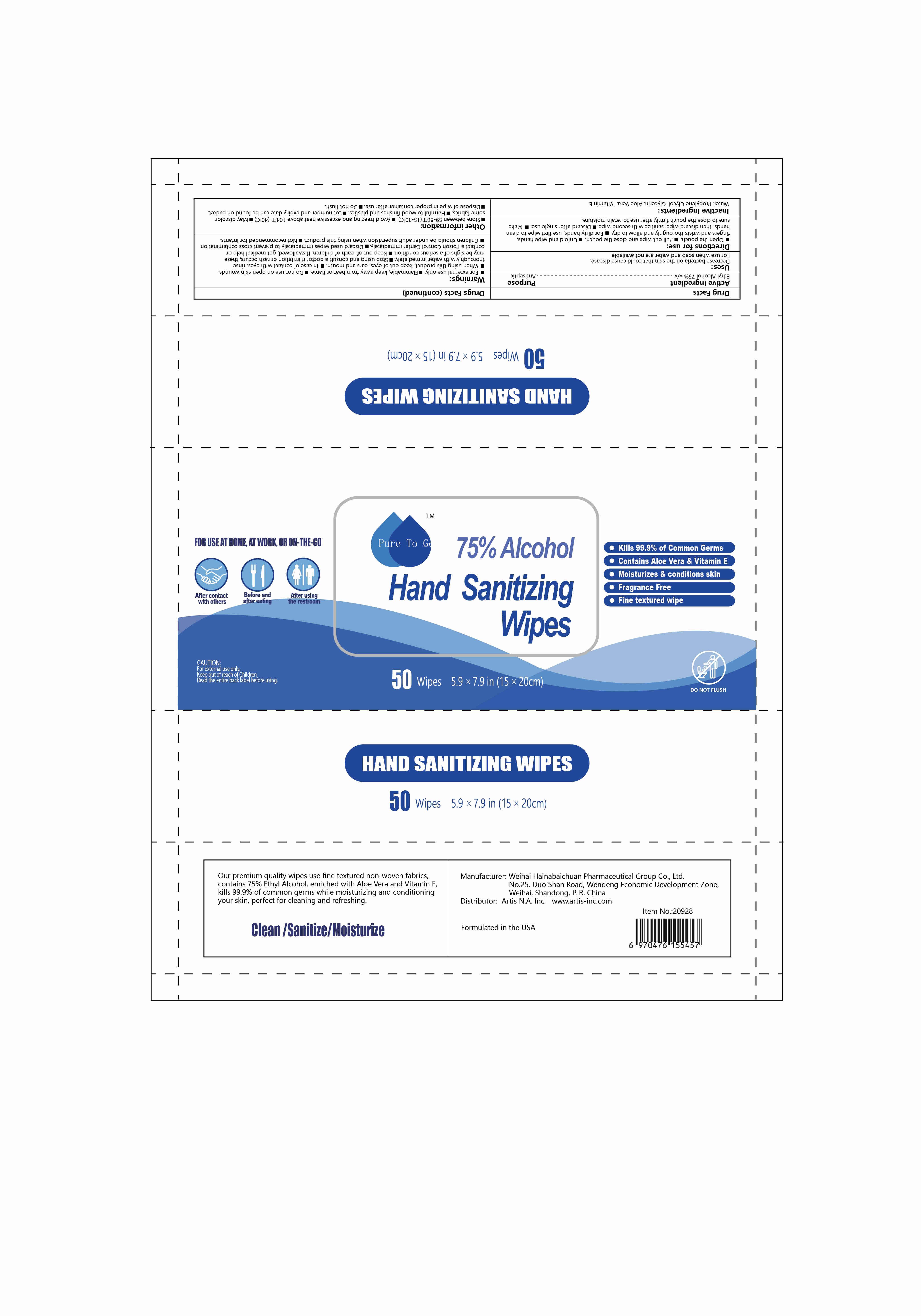 DRUG LABEL: hand sanitizing wipes
NDC: 96386-001 | Form: CLOTH
Manufacturer: WEIHAI HAI NA BAI CHUAN PHARMACEUTICAL GROUP
Category: otc | Type: HUMAN OTC DRUG LABEL
Date: 20200824

ACTIVE INGREDIENTS: ALCOHOL 150 mL/50 1
INACTIVE INGREDIENTS: ALOE VERA LEAF; PROPYLENE GLYCOL; WATER; GLYCERIN; .ALPHA.-TOCOPHEROL

DOSAGE AND ADMINISTRATION

Store between 59-86°F(15-30°C).Avoid freezing and excessive heat above 104°F(40°C)

INACTIVE INGREDIENT

Water,Propylene Glycol,Glycerin,Aloe Vera,VitaminE

INDICATIONS AND USAGE

Open the pouch.Pull out wipe and close the pouch.Unfold and wipe hands,fingers and wrists thoroughly and allow to dry.For dirty hands,use first wipe to clean hands, then discard wipe; sanitize with second wipe.Discard after single use.Make sure to close the pouch firmly after use to retain moisture.

ACTIVE INGREDIENT

ethyl alcohol

keep out of reach of children

PURPOSE

Disinfection
Sterilization
No Rinseing

WARNINGS

For external use only.Flammable, keep away from heat or flame.Do not use on open skin wounds.